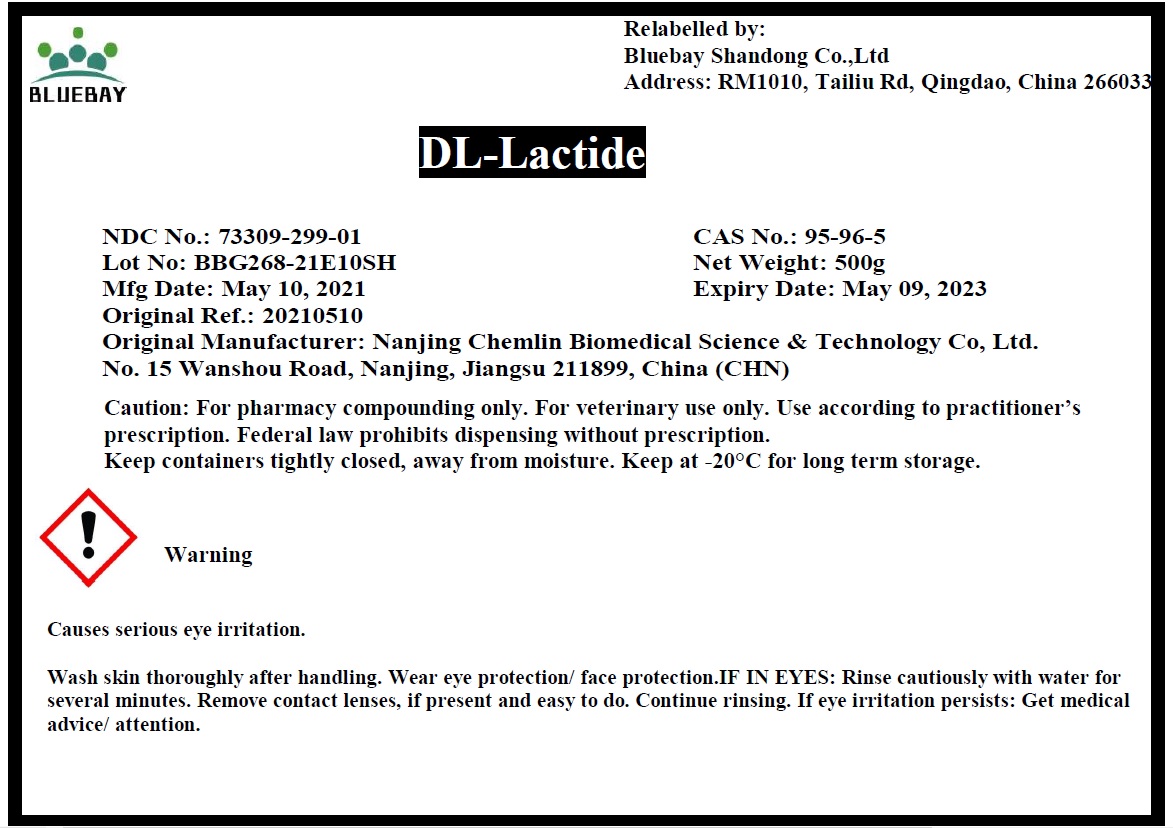 DRUG LABEL: DL-Lactide
NDC: 73309-299 | Form: CRYSTAL
Manufacturer: BLUEBAY SHANDONG CO.,LTD
Category: other | Type: BULK INGREDIENT
Date: 20210601

ACTIVE INGREDIENTS: LACTIDE, DL- 1 g/1 g

DL-Lactide